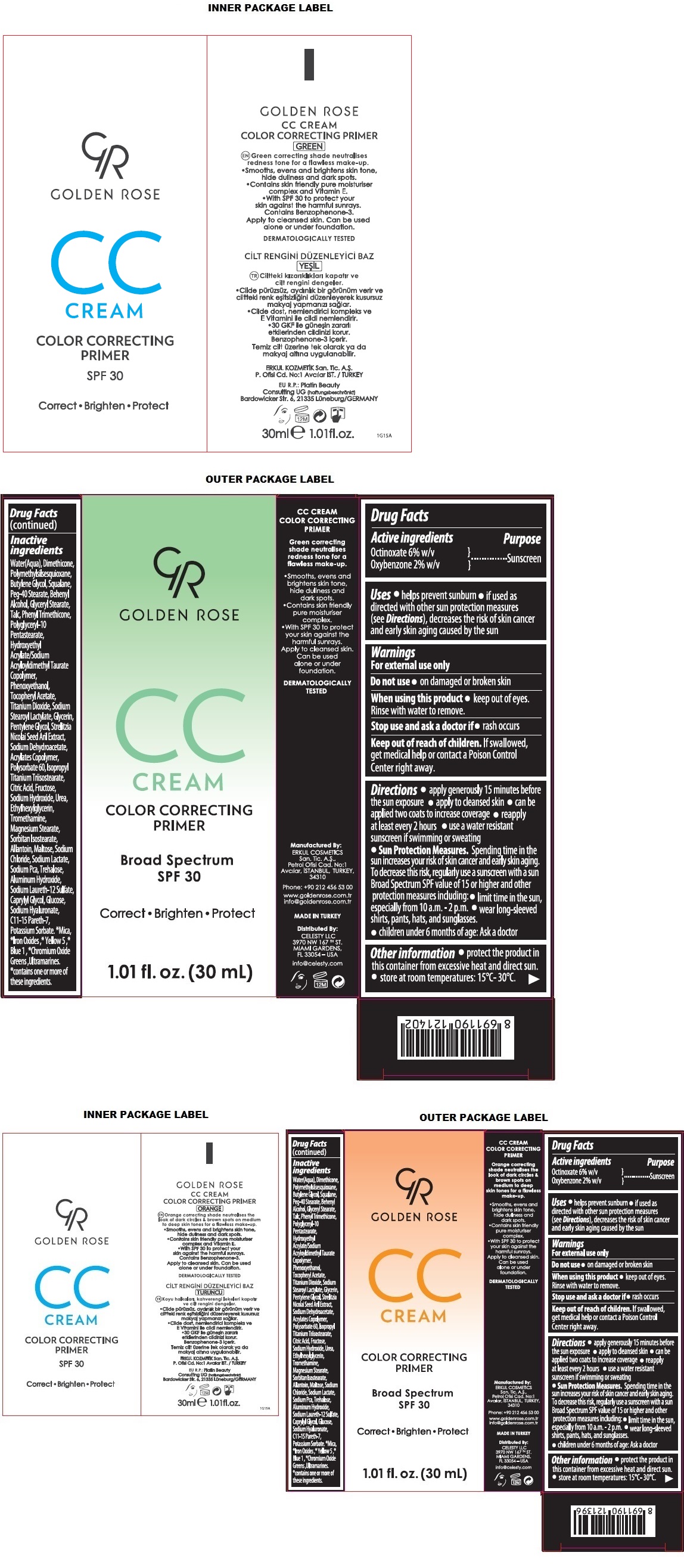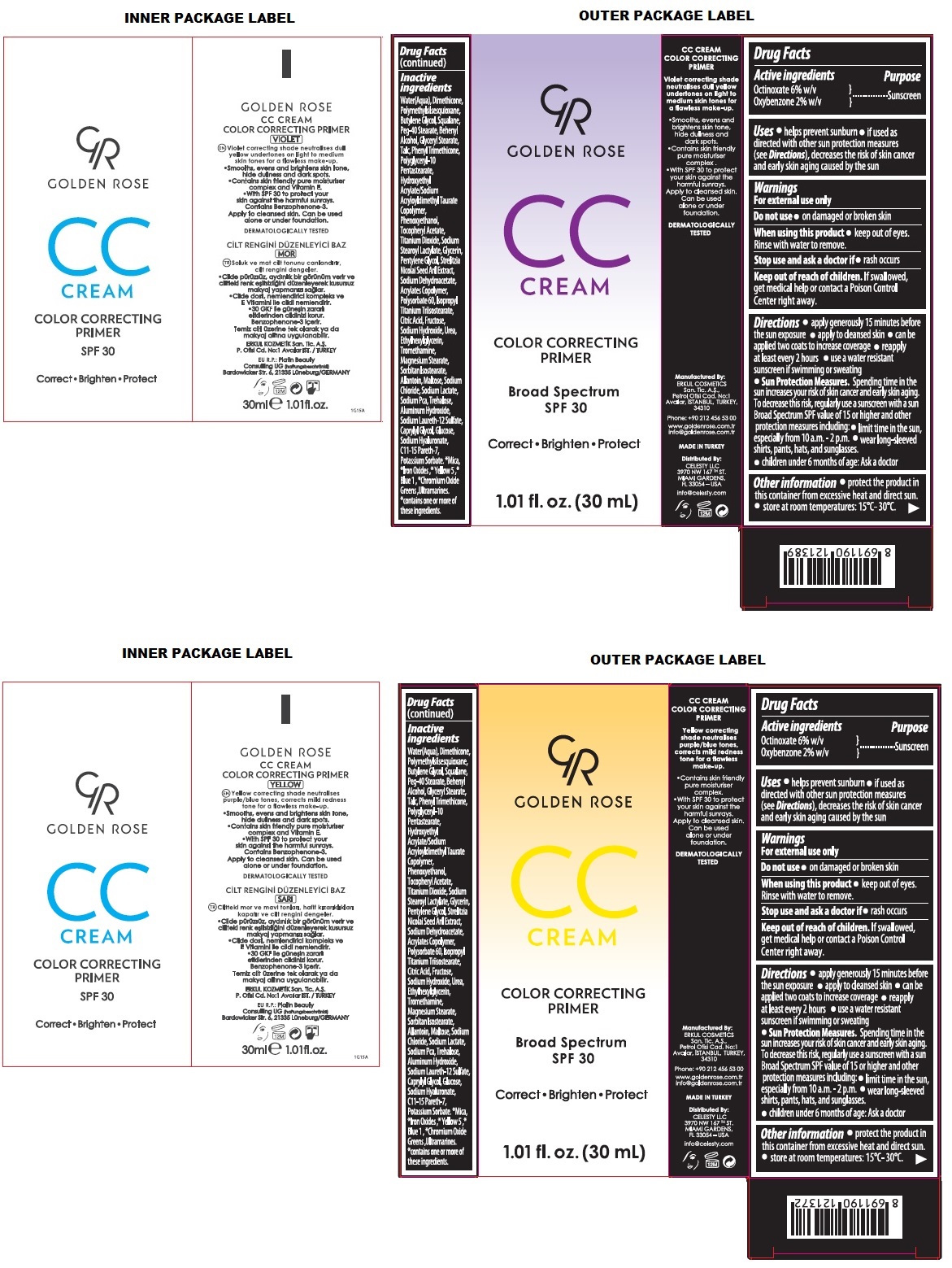 DRUG LABEL: GR CC Broad Spectrum SPF 30
NDC: 82715-102 | Form: CREAM
Manufacturer: ERKUL KOZMETIK SANAYI VE TICARET ANONIM SIRKETI
Category: otc | Type: HUMAN OTC DRUG LABEL
Date: 20250806

ACTIVE INGREDIENTS: OCTINOXATE 6 g/100 mL; OXYBENZONE 2 g/100 mL
INACTIVE INGREDIENTS: WATER; DIMETHICONE, UNSPECIFIED; POLYMETHYLSILSESQUIOXANE (4.5 MICRONS); BUTYLENE GLYCOL; SQUALANE; PEG-40 MONOSTEARATE; DOCOSANOL; GLYCERYL MONOSTEARATE; TALC; PHENYL TRIMETHICONE; POLYGLYCERYL-10 PENTASTEARATE; HYDROXYETHYL ACRYLATE/SODIUM ACRYLOYLDIMETHYL TAURATE COPOLYMER (100000 MPA.S AT 1.5%); PHENOXYETHANOL; .ALPHA.-TOCOPHEROL ACETATE; TITANIUM DIOXIDE; SODIUM STEAROYL LACTYLATE; GLYCERIN; PENTYLENE GLYCOL; STRELITZIA NICOLAI WHOLE; SODIUM DEHYDROACETATE; LUVISET 360; POLYSORBATE 60; ISOPROPYL TITANIUM TRIISOSTEARATE; CITRIC ACID MONOHYDRATE; FRUCTOSE; SODIUM HYDROXIDE; UREA; ETHYLHEXYLGLYCERIN; TROMETHAMINE; MAGNESIUM STEARATE; SORBITAN ISOSTEARATE; ALLANTOIN; MALTOSE, UNSPECIFIED FORM; SODIUM CHLORIDE; SODIUM LACTATE; SODIUM PYRROLIDONE CARBOXYLATE; TREHALOSE; ALUMINUM HYDROXIDE; SODIUM LAURETH-12 SULFATE; CAPRYLYL GLYCOL; ANHYDROUS DEXTROSE; HYALURONATE SODIUM; C11-15 PARETH-7; POTASSIUM SORBATE; MICA; FERRIC OXIDE RED; FERRIC OXIDE YELLOW; FERROSOFERRIC OXIDE; FD&C YELLOW NO. 5; FD&C BLUE NO. 1; CHROMIC OXIDE; ULTRAMARINE BLUE

GR GOLDEN ROSE CC CREAM COLOR CORRECTING PRIMER

Active ingredients

Octinoxate 6% w/v
Oxybenzone 2% w/v

Purpose

Sunscreen

Uses

• helps prevent sunburn • if used as directed with other sun protection measures (see Directions), decreases the risk of skin cancer and early skin aging caused by the sun

Warnings

For external use only

Do not use • on damaged or broken skin

When using this product • keep out of eyes. Rinse with water to remove.

Stop use and ask a doctor if • rash occurs

Keep out of reach of children. If swallowed, get medical help or contact a Poison Control Center right away.

Directions

• apply generously 15 minutes before the sun exposure • apply to cleansed skin • can be applied two coats to increase coverage • reapply at least every 2 hours • use a water resistant sunscreen if swimming or sweating
• Sun Protection Measures. Spending time in the sun increases your risk of skin cancer and early skin aging. To decrease this risk, regularly use a sunscreen with a sun Broad Spectrum SPF value of 15 or higher and other protection measures including: • limit time in the sun, especially from 10 a.m. - 2 p.m. • wear long-sleeved shirts, pants, hats, and sunglasses.
• children under 6 months of age: Ask a doctor

Other information

• protect the product in this container from excessive heat and direct sun. • store at room temperatures: 15°C- 30°C.

Inactive ingredients

Water(Aqua), Dimethicone, Polymethylsilsesquioxane, Butylene Glycol, Squalane, Peg-40 Stearate, Behenyl Alcohol, Glyceryl Stearate, Talc, Phenyl Trimethicone, Polyglyceryl-10 Pentastearate, Hydroxyethyl Acrylate/Sodium Acryloyldimethyl Taurate Copolymer, Phenoxyethanol, Tocopheryl Acetate, Titanium Dioxide, Sodium Stearoyl Lactylate, Glycerin, Pentylene Glycol, Strelitzia Nicolai Seed Aril Extract, Sodium Dehydroacetate, Acrylates Copolymer, Polysorbate 60, Isopropyl Titanium Triisostearate, Citric Acid, Fructose, Sodium Hydroxide, Urea, Ethylhexylglycerin, Tromethamine, Magnesium Stearate, Sorbitan Isostearate, Allantoin, Maltose, Sodium Chloride, Sodium Lactate, Sodium Pca, Trehalose, Aluminum Hydroxide, Sodium Laureth-12 Sulfate, Caprylyl Glycol, Glucose, Sodium Hyaluronate, C11-15 Pareth-7, Potassium Sorbate. *Mica, *Iron oxides, *Yellow 5, * Blue 1, *Chromium Oxide Greens, Ultramarine.
*contains one or more of these ingredients.

GOLDEN ROSE

COLOR CORRECTING PRIMER

Correct • Brighten • Protect

Green correcting shade neutralises redness tone for a flawless make-up.
Orange correcting shade neutralises the look of dark circles & brown spots on medium to deep skin tones for a flawless make-up.
Violet correcting shade neutralises dull yellow undertones on light to medium skin tones for a flawless make-up.
Yellow correcting shade neutralises purple/blue tones corrects mild redness tone for a flawless make-up.

• Smooths, evens and brightens skin tone, hide dullness and dark spots.
• Contains skin friendly pure moisturiser complex.
• With SPF 30 to protect your skin against the harmful sunrays. Apply to cleaned skin. Can be used alone or under foundation.

DERMATOLOGICALLY TESTED

Manufactured By:

ERKUL COSMETICS San. Tic. A.Ş.,
Petrol Ofisi Cad. No:1
Avcılar, Istanbul, Turkey, 34310

Phone: +90 212 456 53 00

www.goldenrose.com.tr
info@goldenrose.com.tr

MADE IN TURKEY

Distributed By:

CELESTY LLC
3970 NW 167TH ST.
MIAMI GARDENS,
FL 33054 – USA

info@celesty.com

EU R.P: Platin Beauty Consulting UG
(haftungsbeschränkt)
Bardowicker Str. 6, 21335
Lüneburg/GERMANY